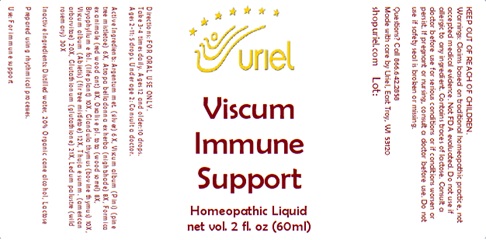 DRUG LABEL: Viscum Immune Support
NDC: 48951-9374 | Form: LIQUID
Manufacturer: Uriel Pharmacy, Inc.
Category: homeopathic | Type: HUMAN OTC DRUG LABEL
Date: 20240903

ACTIVE INGREDIENTS: FORMICA RUFA 8 [hp_X]/1 mL; BOS TAURUS THYMUS 10 [hp_X]/1 mL; ATROPA BELLADONNA 8 [hp_X]/1 mL; LEDUM PALUSTRE TWIG 30 [hp_X]/1 mL; THUJA OCCIDENTALIS WHOLE 20 [hp_X]/1 mL; OXALIS STRICTA WHOLE 8 [hp_X]/1 mL; KALANCHOE DAIGREMONTIANA LEAF 10 [hp_X]/1 mL; VISCUM ALBUM FRUITING TOP 6 [hp_X]/1 mL; GLUTATHIONE 21 [hp_X]/1 mL
INACTIVE INGREDIENTS: WATER; ALCOHOL; LACTOSE, UNSPECIFIED FORM

Viscum Immune Support

INDICATIONS AND USAGE

Directions: FOR ORAL USE ONLY.

DOSAGE AND ADMINISTRATION

Take 3-4 times daily. Ages 12 and older: 10 drops. Ages 2-11: 5 drops. Under age 2: Consult a doctor.

ACTIVE INGREDIENT

Active Ingredients: Viscum album (Pini) (pine tree mistletoe) 6X, Atropa belladonna ex herba (nightshade) 8X, Formica ex animale (red wood ant) 8X, Oxalis e pl. tota (wood sorrel) 8X, Bryophyllum e fol. (life plant) 10X, Glandula thymus (bovine thymus) 10X, Viscum album (Abietis) (fir tree mistletoe) 12X, Thuja e summ. (american arborvitae) 20X, Glutathionum (glutathione) 21X, Ledum palustre (wild rosemary) 30X

INACTIVE INGREDIENT

Inactive Ingredients: Distilled water, 20% Organic cane alcohol, Lactose

Prepared using rhythmical processes

PURPOSE

Uses: For immune support

KEEP OUT OF REACH OF CHILDREN.

WARNINGS

Warnings: Claims based on traditional homeopathic practice, not accepted medical evidence. Not FDA evaluated. Do not use if allergic to any ingredient. Contains traces of lactose. Consult a doctor before use for serious conditions or if conditions worsen or persist. If pregnant or nursing, consult a doctor before use. Do not use if safety seal is broken or missing.

Questions? Call 866.642.2858
Made with care by Uriel, East Troy, WI 53120
shopuriel.com Lot: